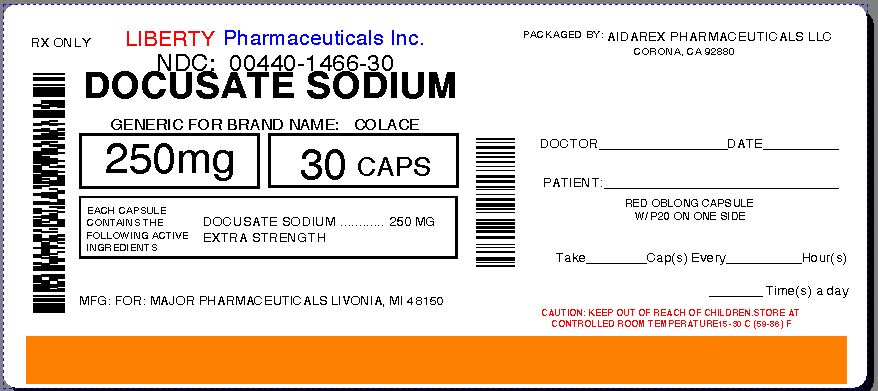 DRUG LABEL: DOK EXTRA STRENGTH STOOL SOFTENER
NDC: 0440-1466 | Form: CAPSULE, LIQUID FILLED
Manufacturer: Liberty Pharmaceuticals, Inc.
Category: otc | Type: HUMAN OTC DRUG LABEL
Date: 20130913

ACTIVE INGREDIENTS: DOCUSATE SODIUM 250 mg/1 1
INACTIVE INGREDIENTS: FD&C RED NO. 40; FD&C YELLOW NO. 6; GELATIN; GLYCERIN; POLYETHYLENE GLYCOLS; PROPYLENE GLYCOL; WATER; SORBITOL

Drug Facts

Active ingredient (in each softgel)

Docusate Sodium 250mg

Purpose

Stool softener

Uses

- for the prevention of dry, hard stools
- for relief of occasional constipation.
- this product generally produces a bowel movement within 12 to 72 hours.

Warnings - Do not use

- if you are taking mineral oil, unless directed by a doctor
- when abdominal pain, nausea, or vomiting are present
- for more than 1 week, unless directed by a doctor

Ask a doctor before use if

you notice a sudden change in bowel habits that persists over a period of 2 weeks

Stop use and ask a doctor if

- you have rectal bleeding
- you fail to have a bowel movement after use

If pregnant or breastfeeding

ask a health professional before use.

Keep out of reach of children.

In case of overdose, get medical help or contact a Poison Control Center right away.

Directions

- adults and children over 12 years of age and over: take 1 softgel daily or as directed by a doctor
- children under 12 years of age: take as directed by a doctor

Other information

- each softgel contains sodium 15mg
- store at controlled room temperature 15o - 30o C (59o- 86o F)
- do not use if imprinted safety seal under cap is broken or missing

Inactive Ingredients

edible white ink, FD&C Red No# 40, FD&C Yellow No. 6, gelatin, glycerin, polyethylene glycol, propylene glycol, purified wter, sorbitol special.

Questions or comments?

Adverse Drug Event Call: (800) 616-2471

Product Labeling

MAJOR DOK™

Docusate Sodium 250 mg

Extra Strength Stool Softener

For use as a Stool Softener in treating & Avoiding Constipation

Distributed by:

Major Pharmaceuticals

31778 Enterprise Drive

Livonia, MI 48150, USA

Repackaged By :
Aidarex Pharmaceuticals LLC,
Corona, CA 92880